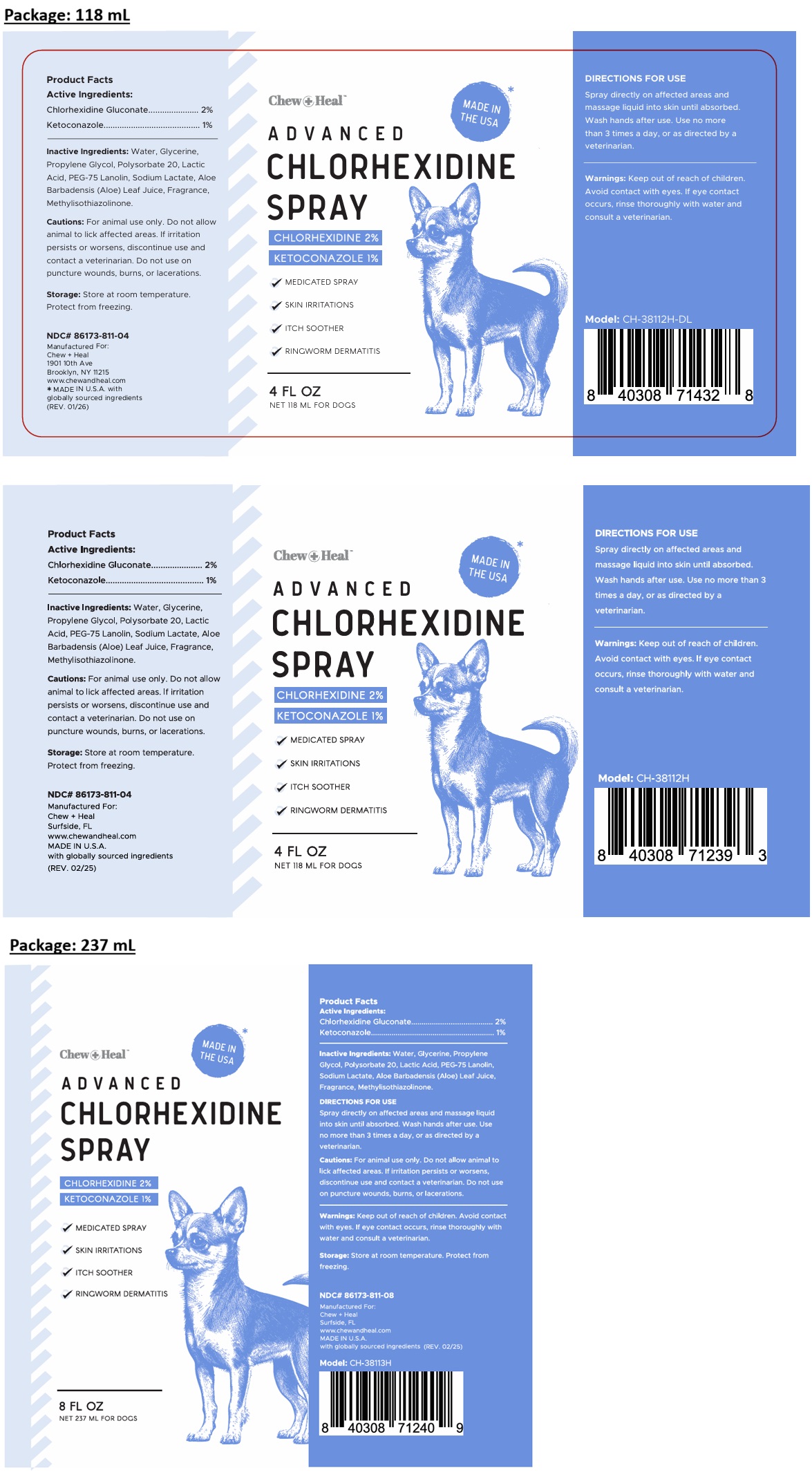 DRUG LABEL: Chew Plus Heal ADVANCED CHLORHEXIDINE
NDC: 86173-811 | Form: SPRAY
Manufacturer: Click Industries LLC
Category: animal | Type: OTC ANIMAL DRUG LABEL
Date: 20260106

ACTIVE INGREDIENTS: CHLORHEXIDINE GLUCONATE 2 g/100 mL; KETOCONAZOLE 1 g/100 mL
INACTIVE INGREDIENTS: WATER; GLYCERIN; PROPYLENE GLYCOL; POLYSORBATE 20; LACTIC ACID, UNSPECIFIED FORM; PEG-75 LANOLIN; SODIUM LACTATE; ALOE VERA LEAF; METHYLISOTHIAZOLINONE

Chew+Heal™ ADVANCED CHLORHEXIDINE SPRAY

Active Ingredients:

Chlorhexidine Gluconate........... 2%
Ketoconazole............................. 1%

Inactive Ingredients:

Water, Glycerine, Propylene Glycol, Polysorbate 20, Lactic Acid, PEG-75 Lanolin, Sodium Lactate, Aloe Barbadensis (Aloe) Leaf Juice, Fragrance, Methylisothiazolinone.

DIRECTIONS FOR USE

Spray directly on affected areas and massage liquid into skin until absorbed. Wash hands after use. Use no more than 3 times a day, or as directed by a veterinarian.

Cautions:

For animal use only. Do not allow animal to lick affected areas. If irritation persists or worsens, discontinue use and contact a veterinarian. Do not use on puncture wounds, burns, or lacerations.

Warnings:

Keep out of reach of children. Avoid contact with eyes. If eye contact occurs, rinse thoroughly with water and consult a veterinarian.

Storage:

Store at room temperature. Protect from freezing.

✓ MEDICATED SPRAY

✓ SKIN IRRITATIONS

✓ ITCH SOOTHER

✓ RINGWORM DERMATITIS

FOR DOGS

Manufactured For:
Chew + Heal
1901 10th Ave
Brooklyn, NY 11215

Manufactured For:
Chew + Heal
Surfside, FL
www.chewandheal.com
MADE IN U.S.A.
with globally sourced ingredients